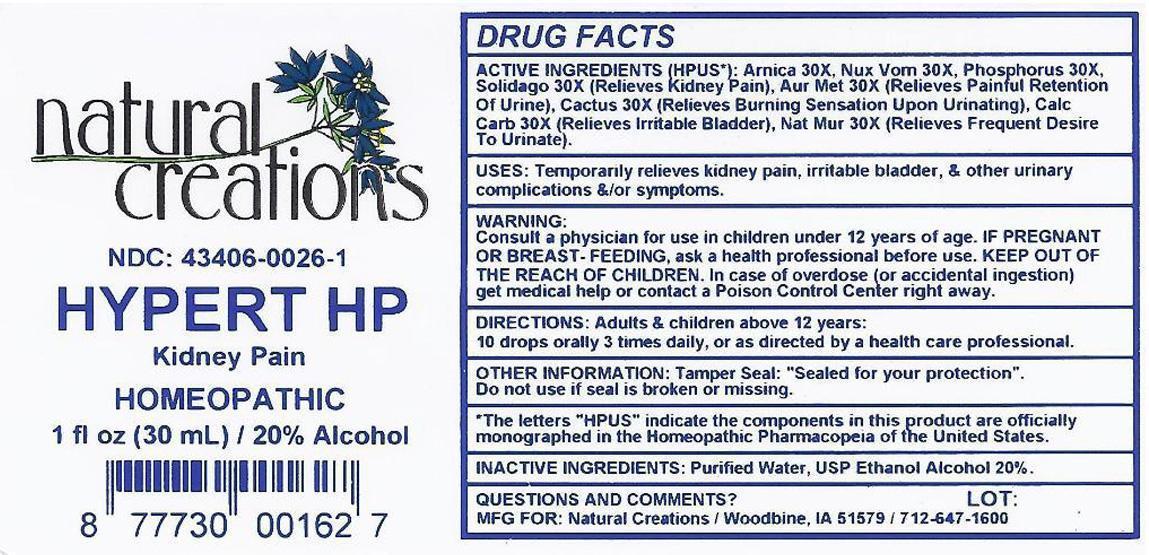 DRUG LABEL: HYPERT HP
NDC: 43406-0026 | Form: LIPSTICK
Manufacturer: Natural Creations, Inc.
Category: homeopathic | Type: HUMAN OTC DRUG LABEL
Date: 20121105

ACTIVE INGREDIENTS: ARNICA MONTANA 30 [hp_X]/1 mL; GOLD 30 [hp_X]/1 mL; SELENICEREUS GRANDIFLORUS STEM 30 [hp_X]/1 mL; OYSTER SHELL CALCIUM CARBONATE, CRUDE 30 [hp_X]/1 mL; SODIUM CHLORIDE 30 [hp_X]/1 mL; STRYCHNOS NUX-VOMICA SEED 30 [hp_X]/1 mL; PHOSPHORUS 30 [hp_X]/1 mL; SOLIDAGO VIRGAUREA FLOWERING TOP 30 [hp_X]/1 mL
INACTIVE INGREDIENTS: WATER; ALCOHOL

HYPERT HP

ACTIVE INGREDIENT

ACTIVE INGREDIENTS (HPUS*): Arnica Montana 30X, Aurum Metallicum 30X, Cactus Grandiflorus 30X, Calcarea Carbonica 30X, Natrum Muriaticum 30X, Nux Vomica 30X, Phosphorus 30X, Solidago Virgaurea 30X

INDICATIONS AND USAGE

USES: Temporarily relieves kidney pain, irritable bladder, & other urinary complications &/or symptoms.

WARNING:

Consult a physician for use in children under 12 years of age. IF PREGNANT OR BREAST-FEEDING, ask a health care professional before use. KEEP OUT OF THE REACH OF CHILDREN. In case of overdose (or accidental ingestion) get medical help or contact a Poison Control Center right away.

DOSAGE AND ADMINISTRATION

DIRECTIONS: Adults and children above 12 years: 10 drops orally 3 times daily, or as directed by a health care professional.

OTHER INFORMATION: Tamper Seal: "Sealed for your protection."

Do not use if seal is broken or missing.

REFERENCES

*The letters "HPUS" indicate the components in the product are officially monographed in the Homeopathic Pharmacopeia of the United States.

INACTIVE INGREDIENTS: Purified Water, USP Ethanol Alcohol 20%

QUESTIONS AND COMMENTS?

MFG FOR: Natural Creations / Woodbine, IA / 51579 712.647.1600

LOT:

PURPOSE

USES: Temporarily relieves kidney pain, irritable bladder, & other urinary complications &/or symptoms.

KEEP OUT OF REACH OF CHILDREN

KEEP OUT OF THE REACH OF CHILDREN. In case of overdose (or accidental ingestion) get medical help or contact a Poison Control Center.

PACKAGE LABEL

NDC: 43406-0026-1

HYPERT HP

Kidney Pain

HOMEOPATHIC

1 fl oz (30 mL) / 20% Alcohol

UPC: 877730001627